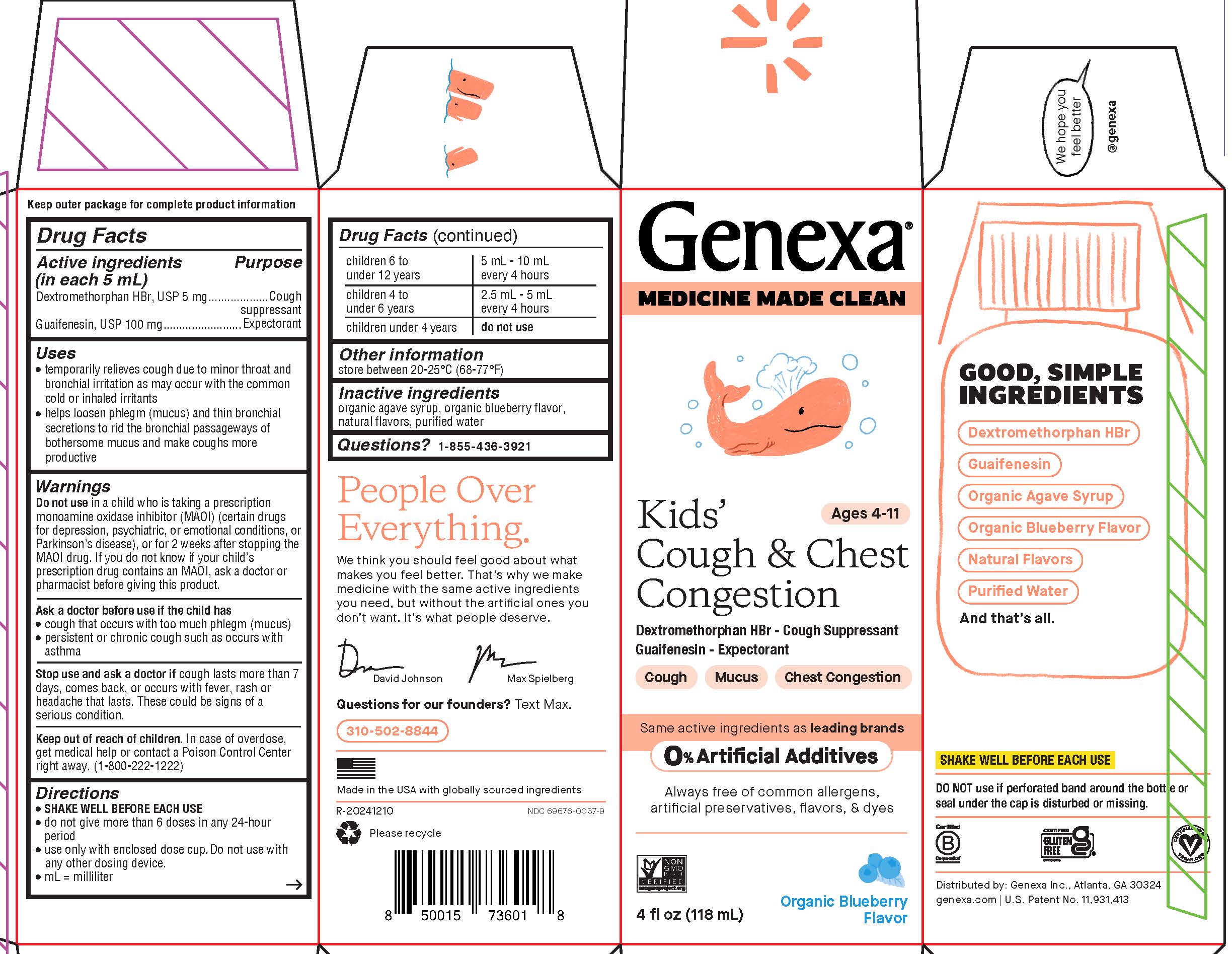 DRUG LABEL: Kids Cough and Chest Congestion
NDC: 69676-0037 | Form: SUSPENSION
Manufacturer: Genexa Inc.
Category: otc | Type: HUMAN OTC DRUG LABEL
Date: 20250801

ACTIVE INGREDIENTS: GUAIFENESIN 100 mg/5 mL; DEXTROMETHORPHAN HYDROBROMIDE 5 mg/5 mL
INACTIVE INGREDIENTS: AGAVE TEQUILANA JUICE; WATER; BLUEBERRY

Kids' Cough & Chest Congestion

Drug Facts

Active ingredients (in each 5 mL)

Dextromethorphan HBr, USP 5 mg

Guaifenesin, USP 100 mg

Purpose

Cough suppressant

Expectorant

Uses

- temporarily relieves cough due to minor throat and bronchial irritation as may occur with the common cold or inhaled irritants
- helps loosen phlegm (mucus) and thin bronchial secretions to rid the bronchial passageways of bothersome mucus and make coughs more productive

Warnings

Do not use in a child who is taking a prescription monoamine oxidase inhibitor (MAOI) (certain drugs for depression, psychiatric, or emotional conditions, or Parkinson’s disease), or for 2 weeks after stopping the MAOI drug. If you do not know if your child’s prescription drug contains an MAOI, ask a doctor or pharmacist before giving this product.

Ask a doctor before use if the child has

- cough that occurs with too much phlegm (mucus)
- persistent or chronic cough such as occurs with asthma

Stop use and ask a doctor if cough lasts more than 7 days, comes back, or occurs with fever, rash or headache that lasts. These could be signs of a serious condition.

Keep out of reach of children. In case of overdose, get medical help or contact a Poison Control Center right away. (1-800-222-1222)

Directions

- SHAKE WELL BEFORE EACH USE
- do not give more than 6 doses in any 24-hour period
- use only with enclosed dose cup. Do not use with any other dosing device.
- mL = milliliter

children 6 to under 12 years | 5 mL - 10 mL every 4 hours
children 4 to under 6 years | 2.5 mL - 5 mL every 4 hours
children under 4 years | do not use

Other information

store between 20-25°C (68-77°F)

Inactive ingredients

organic agave syrup, organic blueberry flavor, natural flavors, purified water

Questions?

1-855-436-3921

SHAKE WELL BEFORE EACH USE

DO NOT use if perforated band around the bottle or seal under the cap is disturbed or missing.

Distributed by: Genexa Inc., Atlanta, GA 30324

genexa.com | U.S. Patent No. 11,931,413

Made in the USA with globally sourced ingredients

NDC 69676-0037-9

Directions

- SHAKE WELL BEFORE EACH USE
- do not give more than 6 doses in any 24-hour period
- use only with enclosed dose cup. Do not use with any other dosing device.
- mL = milliliter

children 6 to under 12 years | 5 mL - 10 mL; every 4 hours
children 4 to under 6 years | 2.5 mL - 5 mL; every 4 hours
children under 4 years | do not use

PACKAGE LABEL

Genexa®

MEDICINE MADE CLEAN
Kids' Cough & Chest Congestion

Ages 4-11

Dextromethorphan HBr - Cough Suppressant

Guaifenesin- Expectorant

Cough

Mucus

Chest Congestion

Same effective active ingredients as leading brands

0% Artificial Additives

Always free of common allergens, artificial preservatives, flavors, & dyes

4 FL OZ (118 mL)

Organic Blueberry Flavor